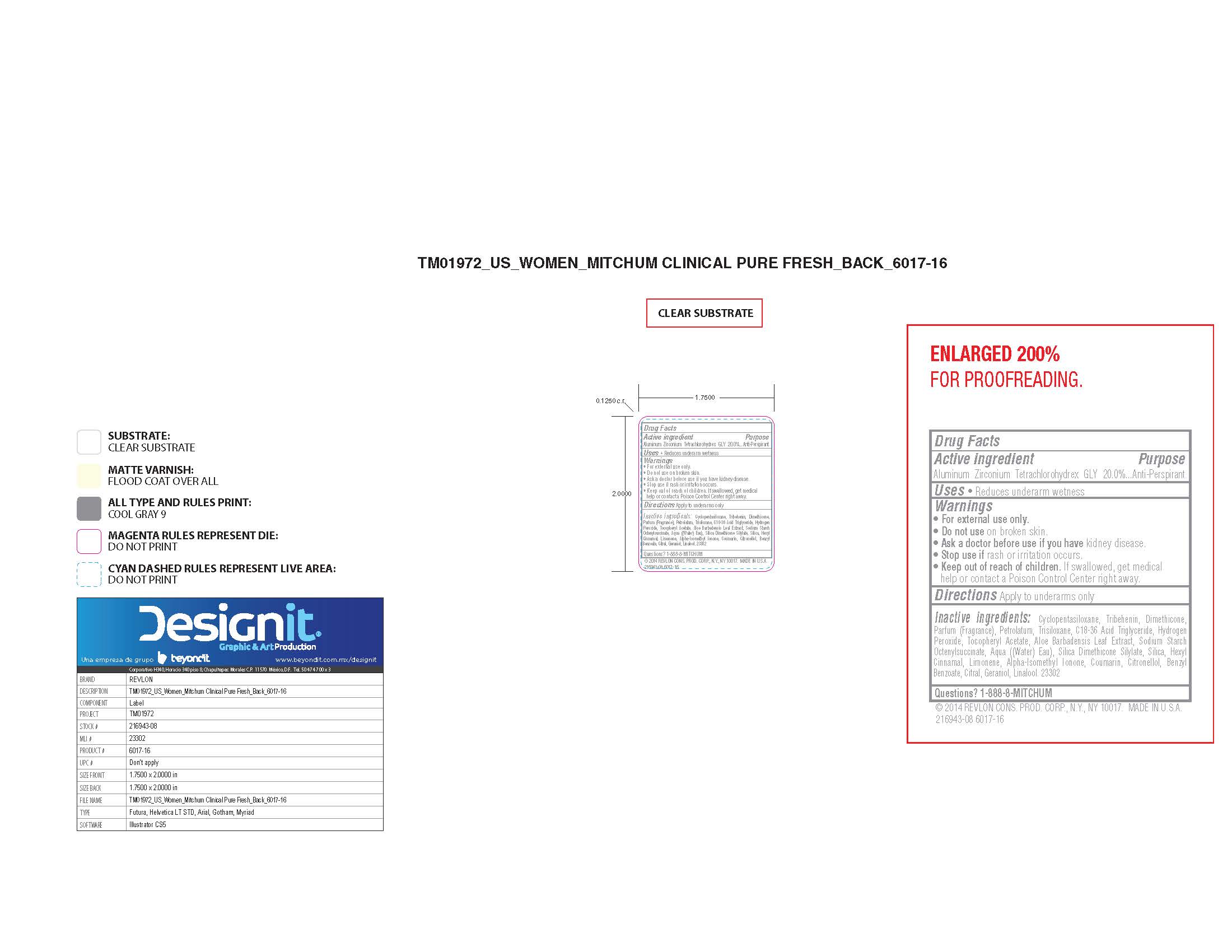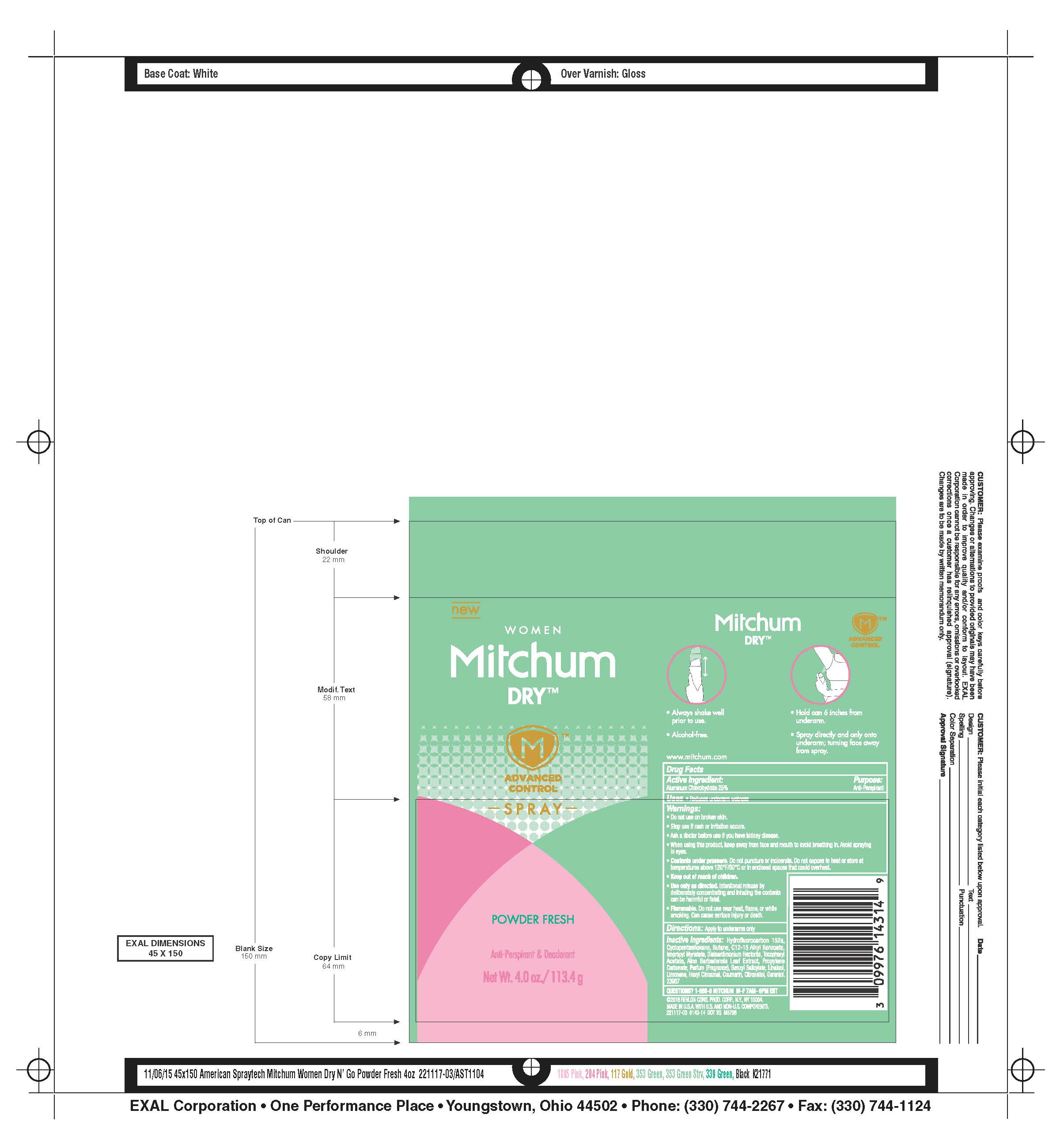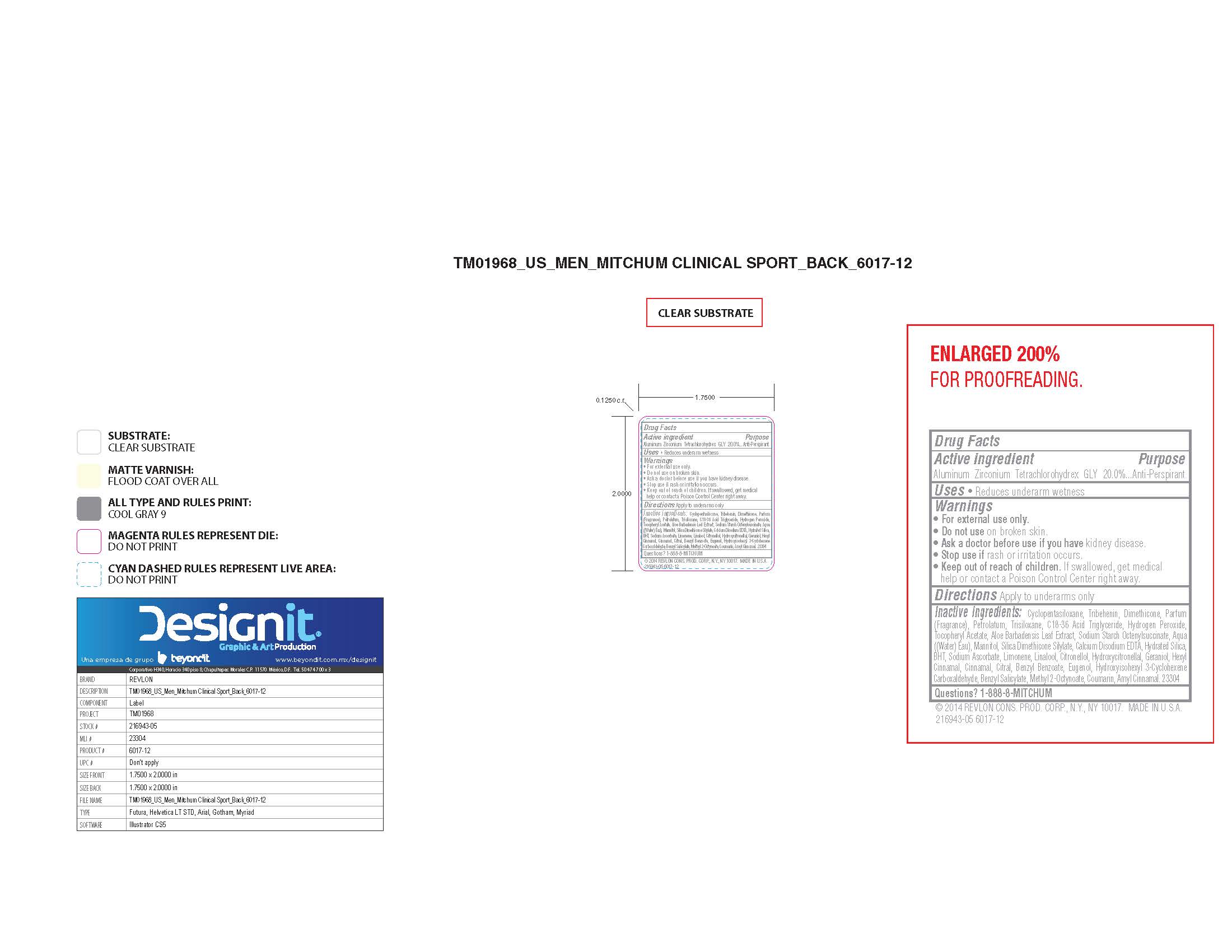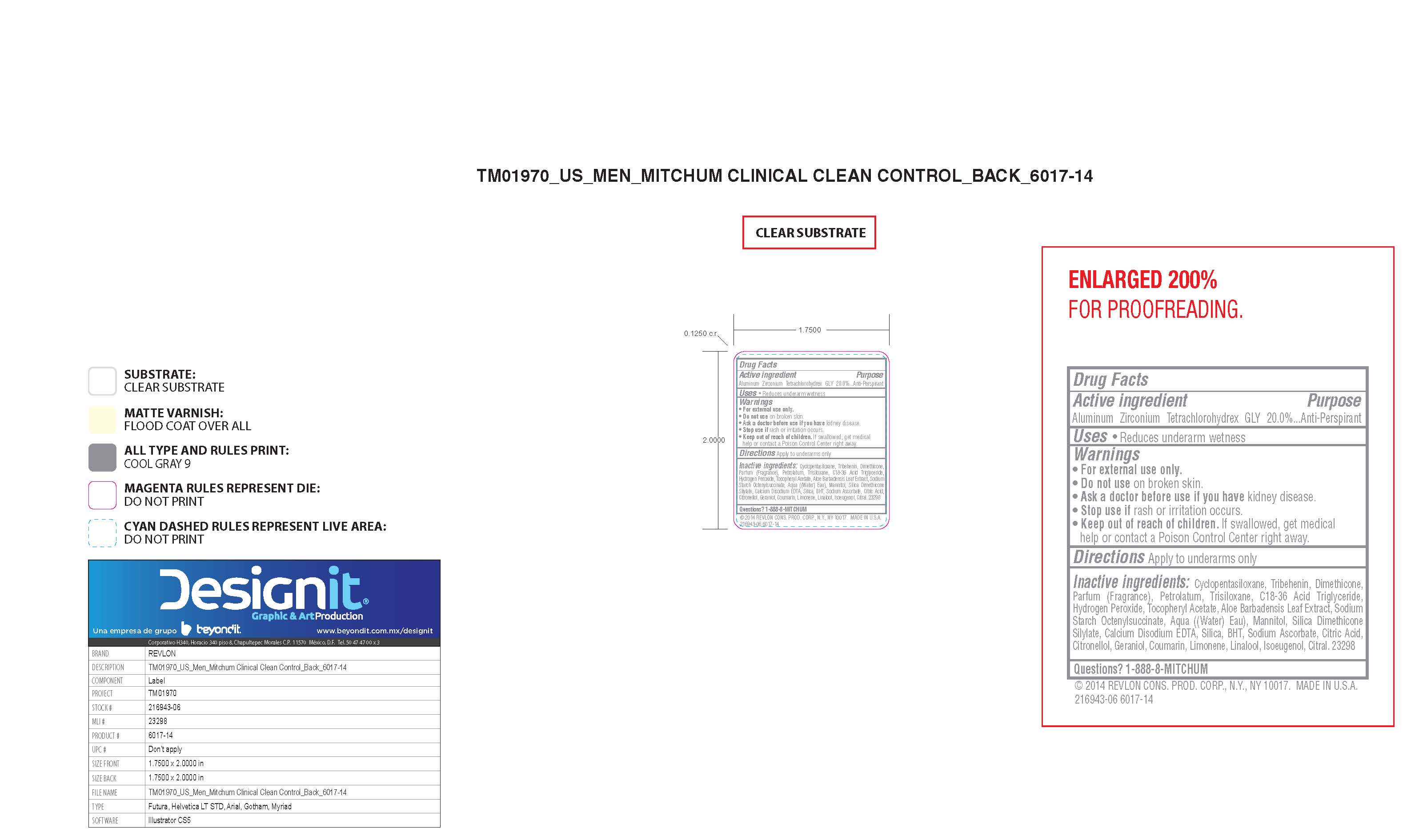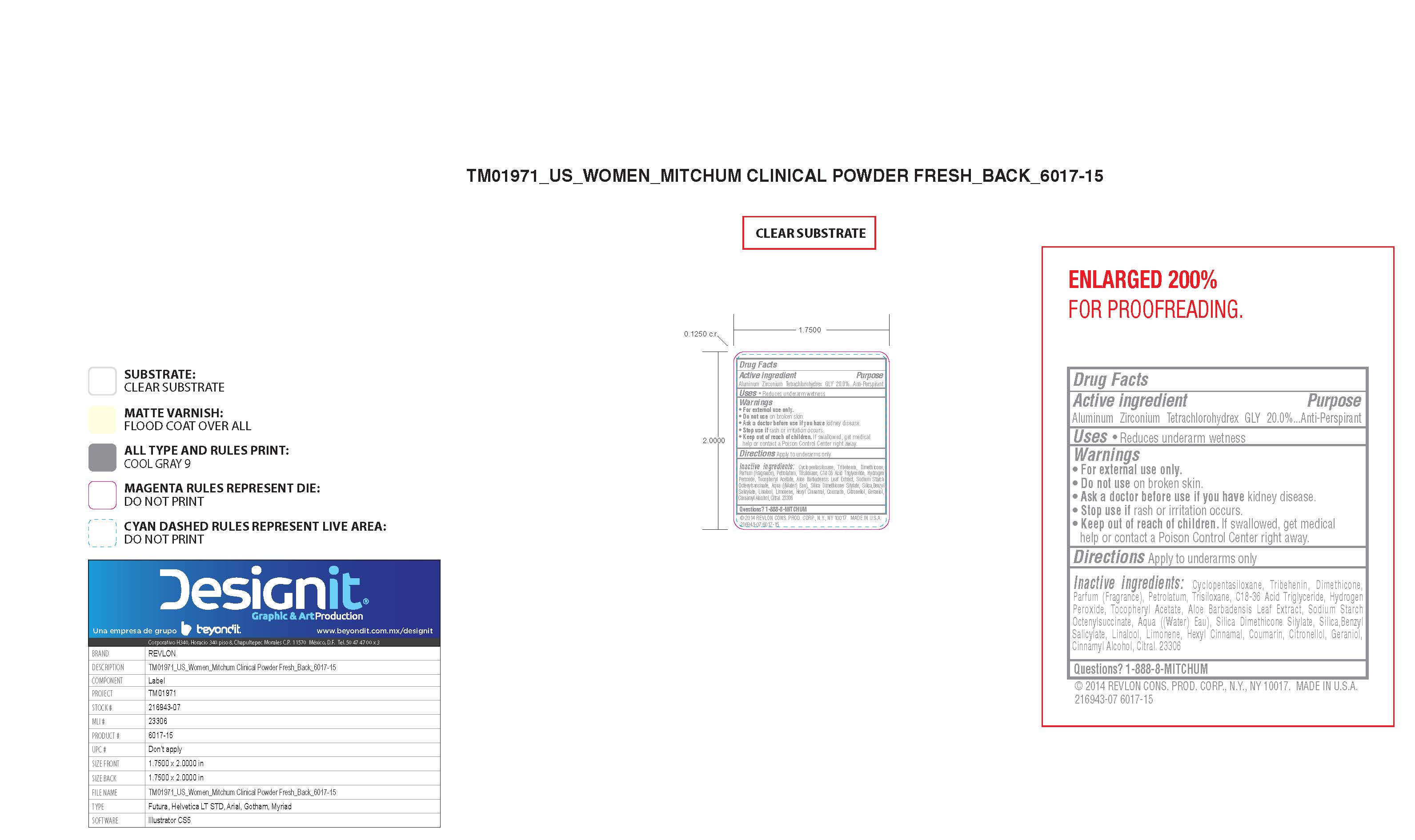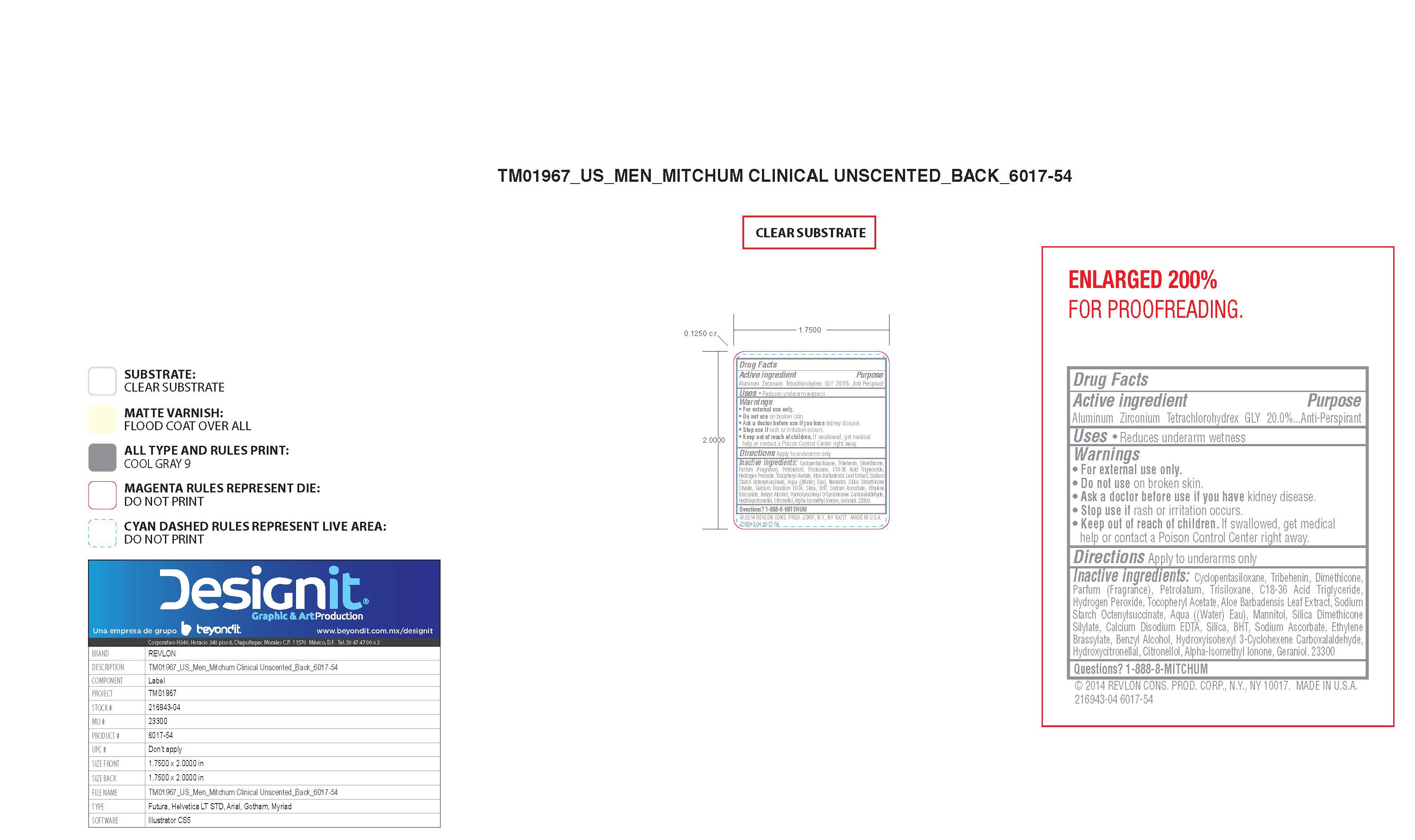 DRUG LABEL: Revlon Mitchum Clinical Strength Soft Solid
NDC: 10967-624 | Form: LIQUID
Manufacturer: Revlon Consumer Products Corp
Category: otc | Type: HUMAN OTC DRUG LABEL
Date: 20161209

ACTIVE INGREDIENTS: ALUMINUM ZIRCONIUM TETRACHLOROHYDREX GLY 0.2 g/1 mL
INACTIVE INGREDIENTS: CYCLOMETHICONE 5; .ALPHA.-TOCOPHEROL ACETATE; ALOE VERA LEAF; MANNITOL; .BETA.-CITRONELLOL, (R)-; GERANIOL; SILICON DIOXIDE; HYDROGEN PEROXIDE; EDETATE CALCIUM DISODIUM ANHYDROUS; SODIUM ASCORBATE; CITRIC ACID MONOHYDRATE; TRIBEHENIN; DIMETHICONE; PETROLATUM; TRISILOXANE; C18-36 ACID TRIGLYCERIDE; ISOPROPYL MYRISTATE; ETHYLENE BRASSYLATE; BENZYL ALCOHOL; HYDROXYISOHEXYL 3-CYCLOHEXENE CARBOXALDEHYDE; HYDROXYCITRONELLAL; ISOMETHYL-.ALPHA.-IONONE; BUTYLATED HYDROXYTOLUENE

Revlon Mitchum Clinical Strength Soft Solid

ACTIVE INGREDIENT

Aluminum Zirconium Tetrachlorohydrex Gly 20%

Purpose

Antiperspirant

Warnings:

For external use only.

Do not use on broken skin

Ask a doctor before use if you have kidney disease

Stop use if rash or irriation occurs

Keep Out of Reach of Children

If swallowed, get medical help or contact a Poison Control Center right away.

Inactive Ingredients

CYCLOPENTASILOXANE, TRIBEHENIN, DIMETHICONE, PETROLATUM, TRISILOXANE, C18-36 ACID TRIGLYCERIDE, AQUA ((WATER) EAU), PARFUM (FRAGRANCE), SODIUM STARCH OCTENYLSUCCINATE, SILICA DIMETHICONE SILYLATE, ISOPROPYL MYRISTATE, ETHYLENE BRASSYLATE, BENZYL ALCOHOL, HYDROGEN PEROXIDE, TOCOPHERYL ACETATE, ALOE BARBADENSIS LEAF EXTRACT, HYDROXYISOHEXYL 3-CYCLOHEXENE CARBOXALDEHYDE, HYDROXYCITRONELLAL, CITRONELLOL, ALPHA-ISOMETHYL IONONE, MANNITOL, SILICA, GERANIOL, BHT, SODIUM ASCORBATE, CITRIC ACID, CALCIUM DISODIUM EDTA

INDICATIONS AND USAGE

Reduces underarm wetness

PACKAGE LABEL

Revlon Mitchum Clinical Strength Soft Solid